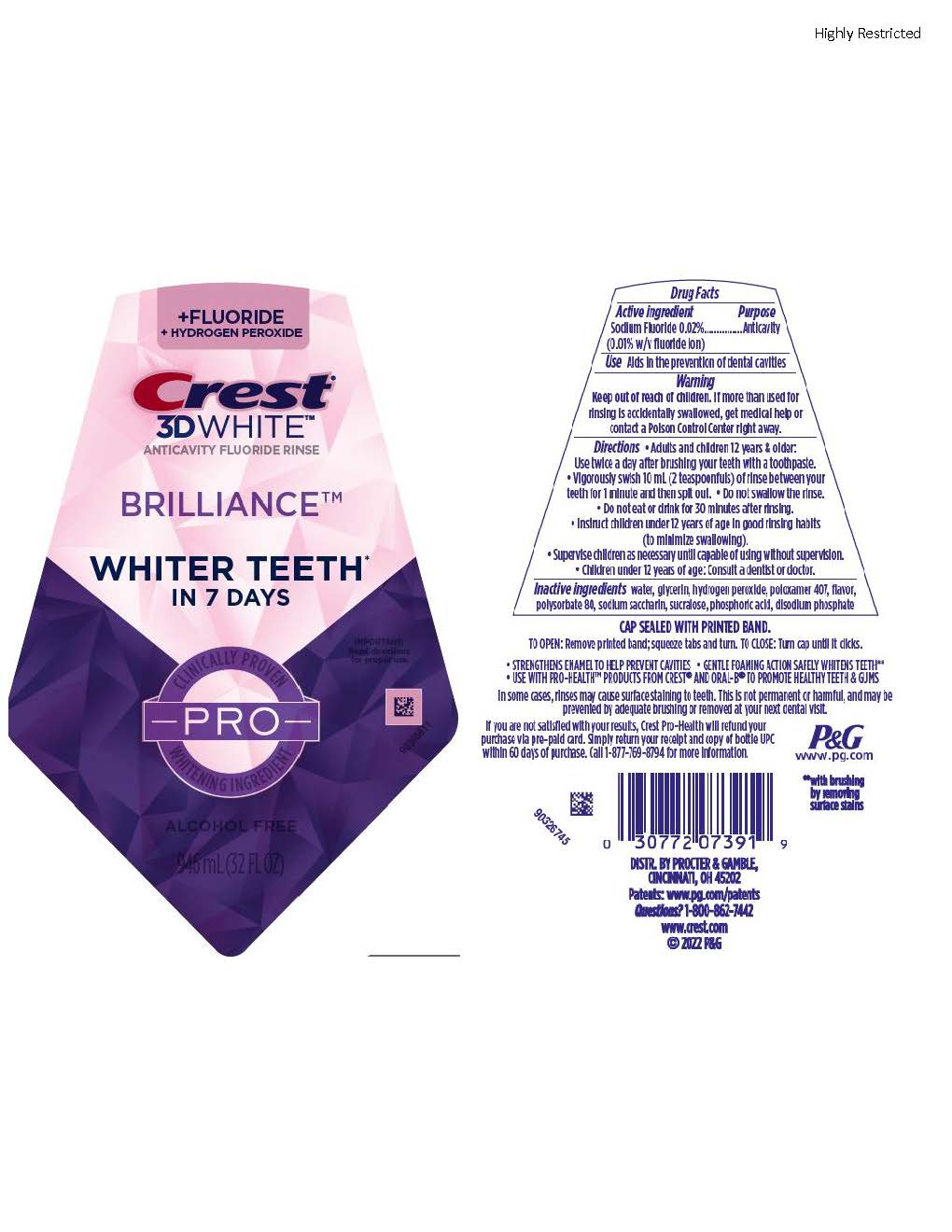 DRUG LABEL: Crest 3D White
NDC: 69423-838 | Form: RINSE
Manufacturer: The Procter & Gamble Manufacturing Company
Category: otc | Type: HUMAN OTC DRUG LABEL
Date: 20250806

ACTIVE INGREDIENTS: SODIUM FLUORIDE 0.1 mg/1 mL
INACTIVE INGREDIENTS: GLYCERIN; HYDROGEN PEROXIDE; POLOXAMER 407; POLYSORBATE 80; SACCHARIN SODIUM; SUCRALOSE; PHOSPHORIC ACID; SODIUM PHOSPHATE, DIBASIC, ANHYDROUS; WATER

Crest 3D White Brilliance Pro Rinse

Drug Facts

Active ingredient

Sodium Fluoride 0.02% (0.01% w/v fluoride ion)

Purpose

Anticavity

Use

Aids in the prevention of dental cavities

Warnings

Keep out of reach of children.If more than used for rinsing is accidentally swallowed, get medical help or contact a Poison Control Center right away.

Directions

- Adults and children 12 years & older:
  - Use twice a day after brushing your teeth with a toothpaste.
  - Vigorously swish 10 mL (2 teaspoonfuls) of rinse between your teeth for 1 minute and then spit out.
  - Do not swallow the rinse.
  - Do not eat or drink for 30 minutes after rinsing.
  - Instruct children under 12 years of age in good rinsing habits (to minimize swallowing).
  - Supervise children as necessary until capable of using without supervision.
- Children under 12 years of age: consult a dentist or doctor.

Inactive ingredients

water, glycerin, hydrogen peroxide, poloxamer 407, flavor, polysorbate 80, sodium saccharin, sucralose, phosphoric acid, disodium phosphate

Questions?

1-800-862-7442

DISTR. BY PROCTER & GAMBLE,
CINCINNATI, OH 45202

PRINCIPAL DISPLAY PANEL - 946 mL Bottle Label

+ FLUORIDE

+ HYDROGEN PEROXIDE

Crest

3D WHITE

ANTICAVITY FLOURIDE RINSE

BRILLIANCE

WHITER TEETH

IN 7 DAYS

IMPORTANT:

Read directions

for proper use.

CLINICALLY PROVEN

PRO
WHITENING INGREDIENT

ALCOHOL FREE

946mL (32 FL OZ)